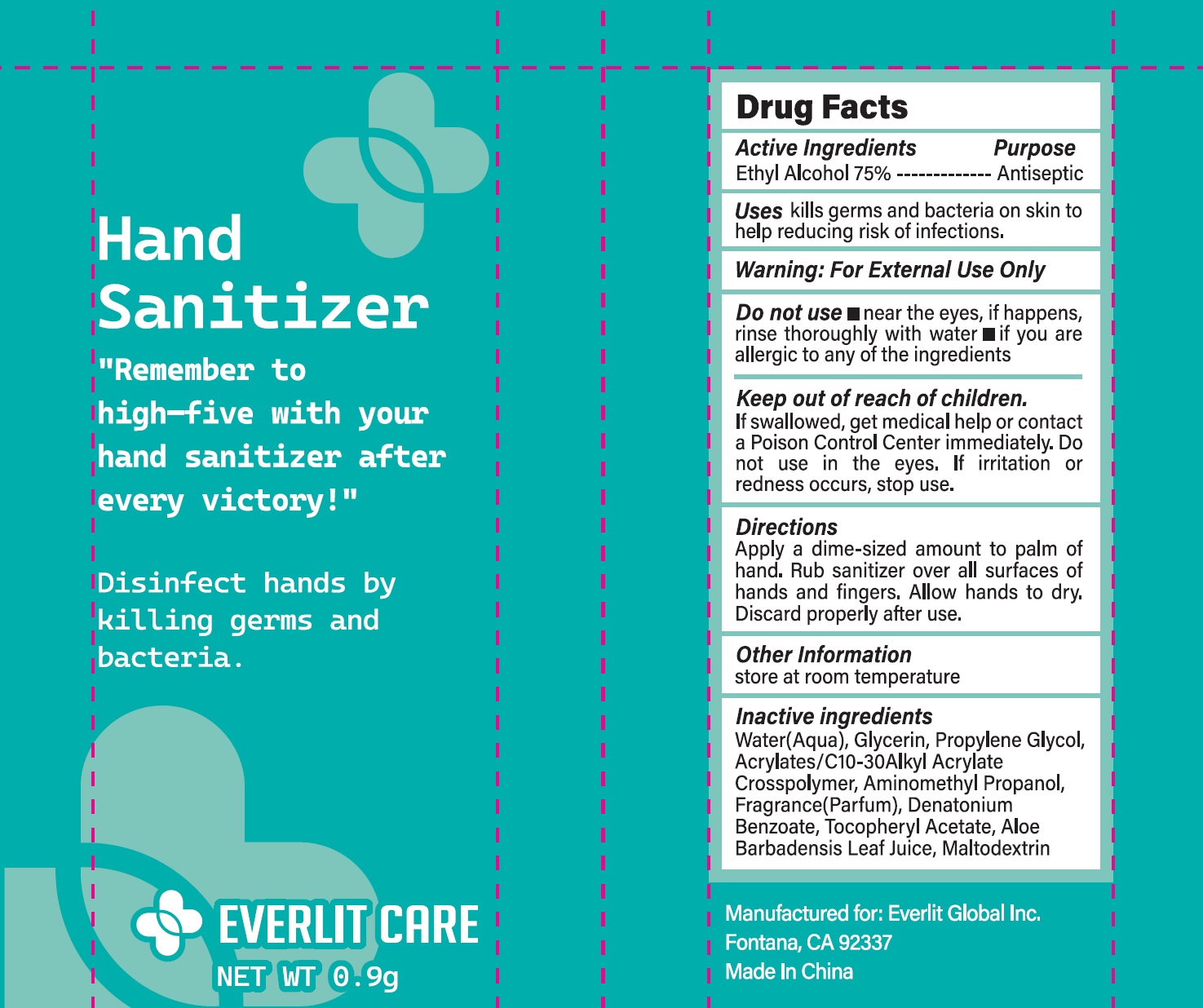 DRUG LABEL: EVERLIT CARE Hand Sanitizer
NDC: 83807-001 | Form: GEL
Manufacturer: EVERLIT GLOBAL INC.
Category: otc | Type: HUMAN OTC DRUG LABEL
Date: 20231114

ACTIVE INGREDIENTS: ALCOHOL 75 mL/100 mL
INACTIVE INGREDIENTS: WATER; GLYCERIN; PROPYLENE GLYCOL; ACRYLATES/C10-30 ALKYL ACRYLATE CROSSPOLYMER (60000 MPA.S); TOCOPHERYL GLUCOSIDE; AMINOMETHYLPROPANOL; DENATONIUM BENZOATE; MALTODEXTRIN; ALOE

83807-001 sanitizer

Active ingredient

Ethyl Alcohol, 75% v/v

Purpose Antiseptic

Uses

Kill germs and bacteria on skin to help reducing risk of infections

Warnings

For external use only.

Flammable, keep away from fire or flame.

Do not use

near the eyes, if happens, rinse thoroughly with water.

if you are allergic to any of the ingredients

Stop use and ask a doctor if

irritation, excessive redness

or rash develops.

Keep out of reach of children. If swallowed, get medical help or contact a Poison Control Center immediately.

Do not use in the eyes. If irritation or redness occurs, stop use.

Directions

Apply a dime sized amount to palm of hand. Rub santizer all over surface of hands and fingers. Allow hands to dry. Discard properly after use.

Other information

Store at room temperature

Inactive ingredients

water, glycerin, propylene glycol, acrylates/ C10-C30 alkyl acrylate crossploymer, aminomethyl propanol, fragrance, denatonium benzoate, tocopheryl acetate, aloe barbadensis leaf jiuce, maltodextrin